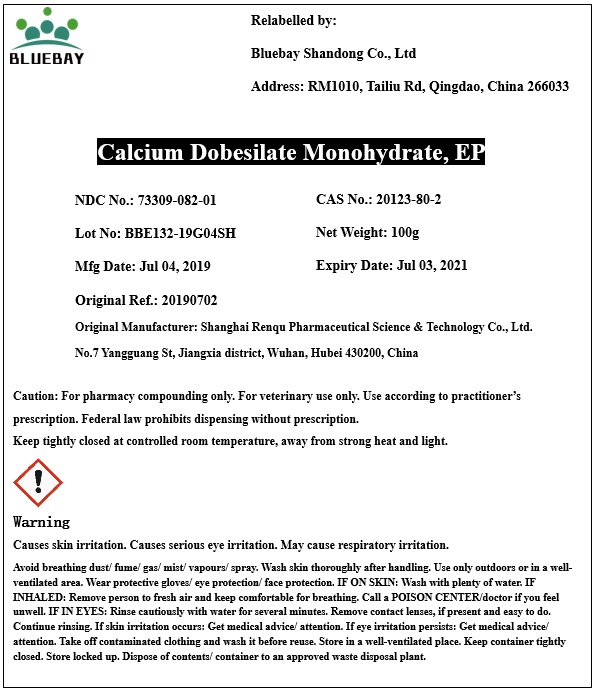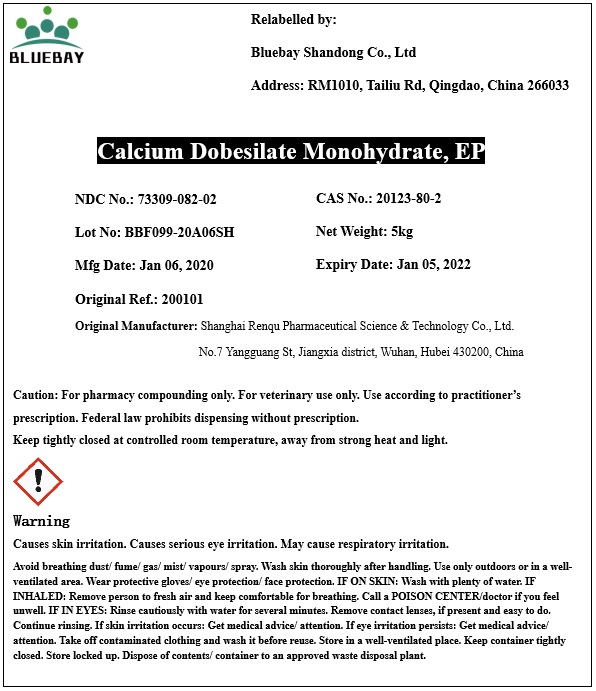 DRUG LABEL: Calcium dobesilate monohydrate
NDC: 73309-082 | Form: POWDER
Manufacturer: BLUEBAY SHANDONG CO.,LTD
Category: other | Type: BULK INGREDIENT
Date: 20200326

ACTIVE INGREDIENTS: CALCIUM DOBESILATE 1 g/1 g

Calcium dobesilate monohydrate